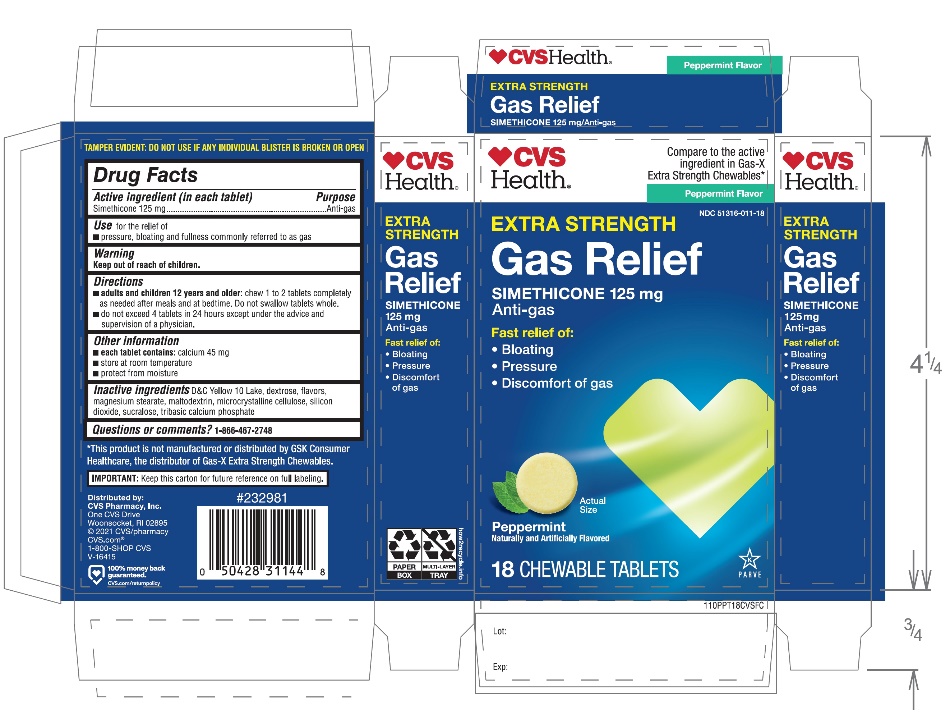 DRUG LABEL: CVS PHARMACY

NDC: 51316-011 | Form: TABLET, CHEWABLE
Manufacturer: CVS
Category: otc | Type: HUMAN OTC DRUG LABEL
Date: 20251208

ACTIVE INGREDIENTS: DIMETHICONE, UNSPECIFIED 125 mg/1 1
INACTIVE INGREDIENTS: D&C YELLOW NO. 10; DEXTROSE, UNSPECIFIED FORM; MAGNESIUM STEARATE; MALTODEXTRIN; MICROCRYSTALLINE CELLULOSE; SILICON DIOXIDE; SUCRALOSE; TRIBASIC CALCIUM PHOSPHATE

CVS Extra Strength Gas Relief Tablets

Active Ingredient (in each tablet)

Simethicone 125 mg

PURPOSE

Anti-gas

Use

For the relief of:

- Pressure, bloating and fullness commonly referred to as gas

Directions

- adults and children 12 years and older:chew 1 to 2 tablets completely as needed after meals and at bedtime, Do not swallow tablets whole.
- do not exceed 4 tablets in a 24 hour period except under the advice and supervision of a physician

Other Information

- each tablet contains:calcium 45 mg
- store at room temperature
- protect from moisture

Inactive Ingredients

D&C yellow # 10, dextrose, flavors, magnesium stearate, microcrystalline cellulose, silicon dioxide, sucralose, tribasic calcium phosphate

Questions or comments

1-866-467-2748

Principal Display Panel

*Compare to the active ingredient in Gas-X Extra Strength
NDC 51316-011-18
Extra strength
Gas Relief
Simethicone 125 mg/Anti-Gas
Fast Relief of Pressure, Bloating & Discomfort

Peppermint Flavor

Naturally and Artificially Flavored

18 Chewable Tablets

*This product is not manufactured or distributed by GSK Consumer Healthcare, the distributor of Gas-X Extra Strength.

IMPORTANT: Keep this carton for future reference on full labeling.